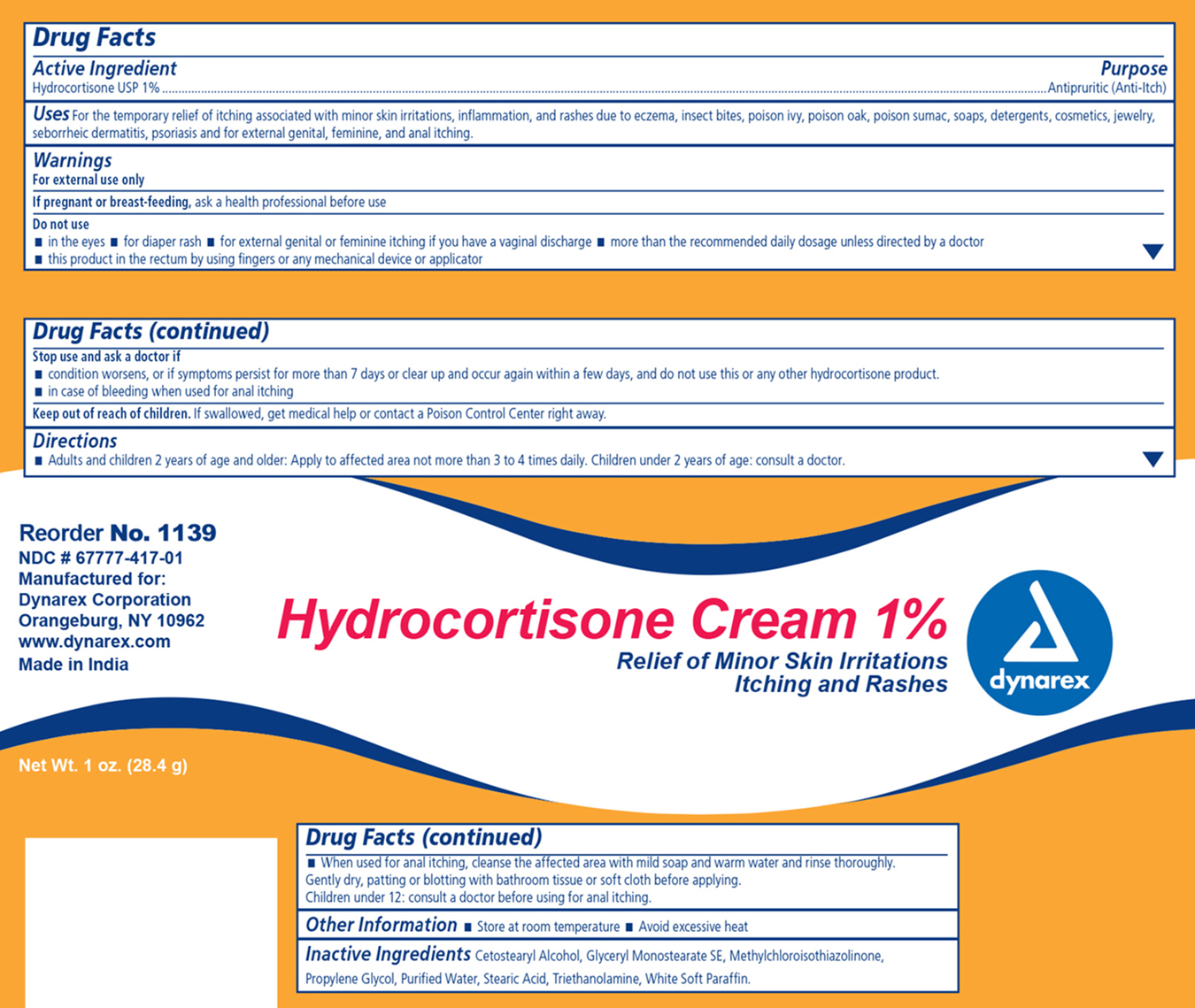 DRUG LABEL: Hydrocortisone
NDC: 67777-417 | Form: CREAM
Manufacturer: Dynarex Corporation
Category: otc | Type: HUMAN OTC DRUG LABEL
Date: 20170623

ACTIVE INGREDIENTS: HYDROCORTISONE 1 g/100 g
INACTIVE INGREDIENTS: PROPYLENE GLYCOL; WATER; STEARIC ACID; CETOSTEARYL ALCOHOL; PARAFFIN; GLYCERYL MONOSTEARATE; METHYLCHLOROISOTHIAZOLINONE; TROLAMINE

Dynarex Hydrocortisone Cream 1%

Active ingredient Purpose

Hydrocortisone 1% Antipruritic (anti-itch)

Warnings

For external use only

Purpose

Uses: For temporary relief of itching associated with minor skin irritations, inflammation, and rashes due to, eczema, insect bites, poison ivy, poison oak, poison sumac, soaps, detergents, cosmetics, jewelry, seborrheic dermatitis, psoriasis and external genital, feminine, and anal itching.

Do Not Use:

- in the eyes
- longer than 1 week unless directed by a physician
- for diaper rash
- if you have vaginal discharge
- more than recommended daily dosage unless directed by a doctor
- in the rectum using fingers or any other mechanical device or applicator

Stop use and ask a doctor if:

- condition worsens, or if symptoms persist for more than 7 days or clear up and occur again within a few days, do not use this or any other hydrocortisone product.
- in case of bleeding when used for anal itching

Keep Out Of Reach of Children

- if swallowed, get medical help or contact a Poison Control Center right away.

Directions:

Adults and children 2 years of age and older:

- apply evenly to affected area no more than 3 or 4 times daily. Children under 2 years of age consult a doctor

- when used for anal itching, cleanse the affected area with mild soap and warm water and rinse thoroughly. Gently dry, patting and blotting with bathroom tissue or soft cloth before applying. Children under 12: consult doctor before using for anal itching.

Inactive ingredients:

Cetostearyl alcohol, glyceryl monostearate, methylchloroisothiazolinone, propylene glycol, purified water, stearic acid, trolamine, white soft paraffin

Other information:

- store at room temperature
- avoid excessive heat

INDICATIONS AND USAGE

For temporary relief of minor skin irritations and external itching.

PACKAGE LABEL

Principal Display Panel

Dynarex Hydrocortisone Items 1137 and 1139

Hydro 1139.jpg